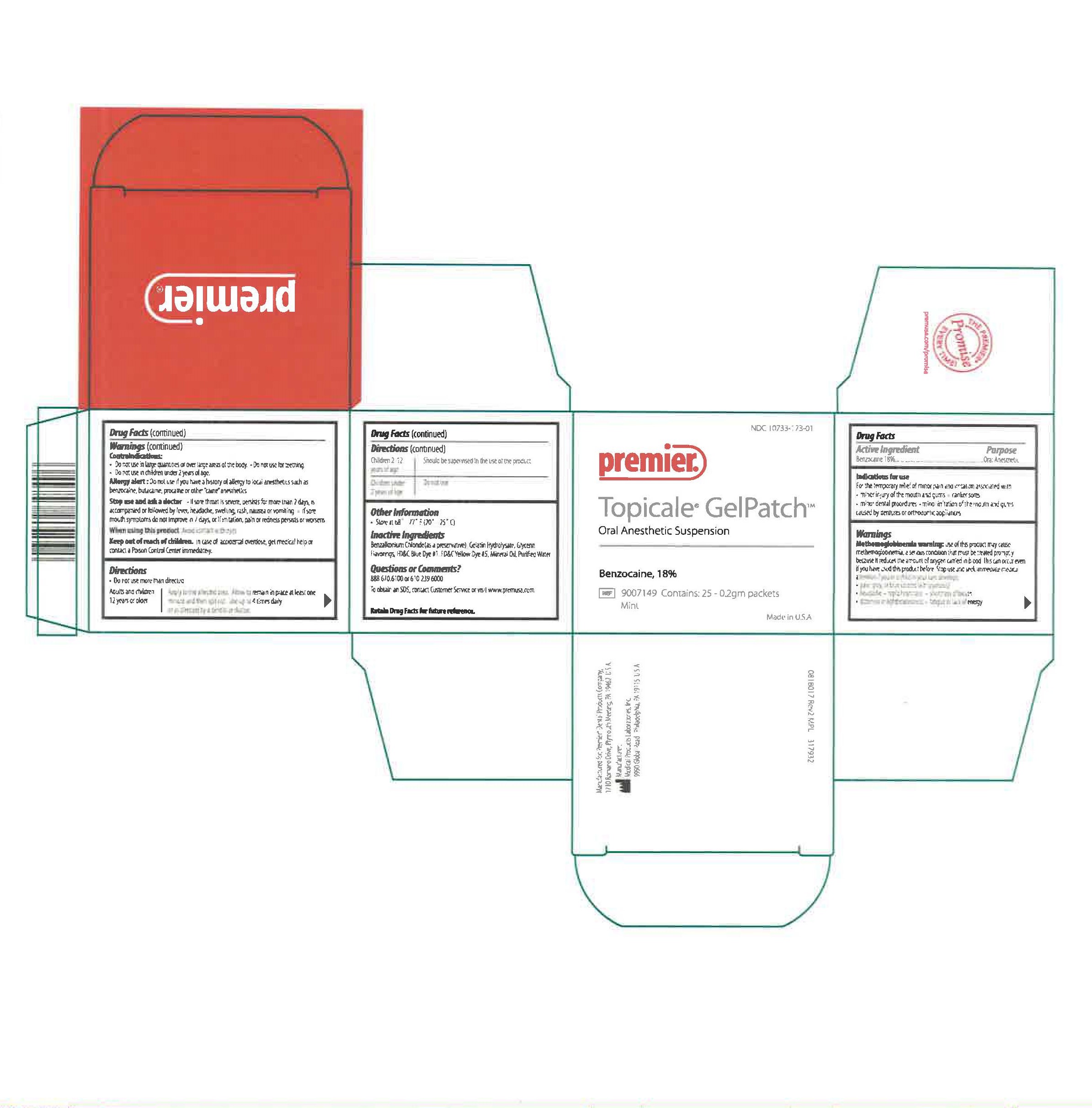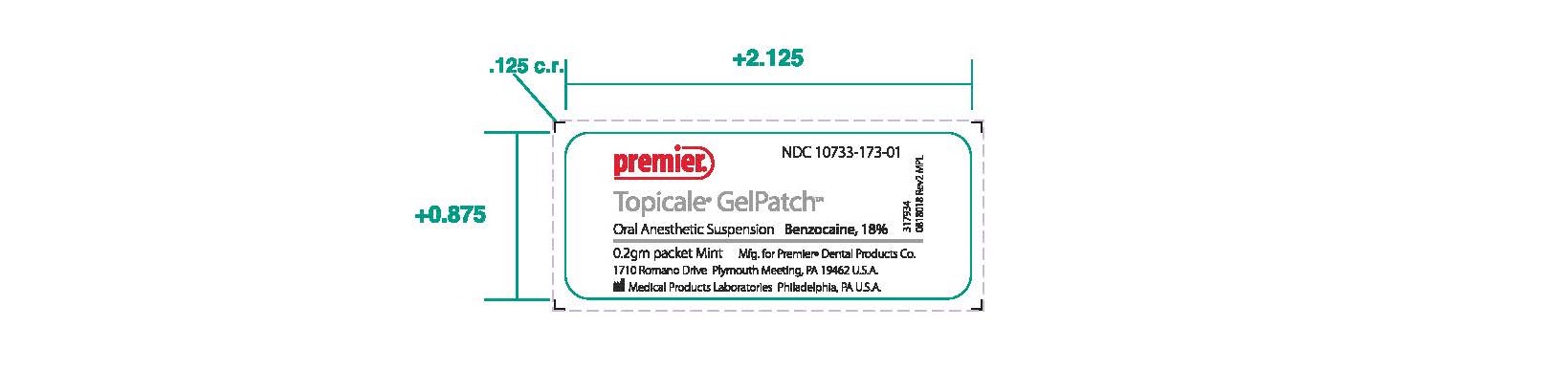 DRUG LABEL: Topicale
NDC: 10733-173 | Form: PATCH
Manufacturer: Medical Products Laboratories, Inc.
Category: otc | Type: HUMAN OTC DRUG LABEL
Date: 20241216

ACTIVE INGREDIENTS: BENZOCAINE 180 mg/1 g
INACTIVE INGREDIENTS: GELATIN HYDROLYSATE (PORCINE SKIN, MW 3000); FD&C YELLOW NO. 5; MINERAL OIL; WATER; GLYCERIN; BENZALKONIUM CHLORIDE; FD&C BLUE NO. 1

Topicale GelPatch

Active Ingredient

Benzocaine 18%

PURPOSE

Oral Anesthetic

INDICATIONS AND USAGE

For the temporary relief of minor pain and irritation associated with minor injury of the mouth and gums, canker sores, minor dental procedures, minor irritation of the mouth and gums caused by dentures or orthodontic appliances

WARNINGS

Methemoglobinemia warning:

Use of this product may cause methemoglobinemia, a serious condition that must be treated promptly because it reduces the amount of oxygen carried in blood. This can occur even if you have used this product before. Stop use and seek immediate medical attention if you or a child in your care develops pale, grey or blue colored skin (cyanosis), headache, rapid heart rate, shortness of breath, dizziness or lightheadedness, fatigue or lack of energy.

Contraindications:

- Do not use in large quantities or over large areas of body
- Do not use for Teething
- Do not use in children under 2 years of age

Allergy Alert:

Do not use if you have a history of allergy to local anesthetics such as benzocaine, butacaine, procaine or other "caine" anesthetics.

When using this product

Avoid contact with eyes

KEEP OUT OF REACH OF CHILDREN

In case of accidental overdose, get medical help or contact a Poison Control Centre immediately.

Stop use and ask a doctor :

If sore throat is severe, persists for more than 2 days, is accompanied or followed by fever, headache, swelling, rash, nausea or vomiting
If sore mouth symptoms do not improve in 7 days, or if irritation, pain or redness persists or worsens

- Do not use more than directed.

Adults and children 12 years or older - Apply to the affected area. Allow to remain in place at least one minute and the spit out. Use up to 4 times daily or as directed by a dentist or doctor.

Children 2-12 years of age - Should be supervised in the use of the product

Children under 2 years of age - Do not use

OTHER SAFETY INFORMATION

- Store at 68º to 77º F (20º - 25º C)

INACTIVE INGREDIENT

Benzalkonium Chloride (as a preservative), Gelatin Hydrolysate, Glycerin, Flavorings,FD&C Blue Dye # 1, FD&C Yellow Dye # 5, Mineral Oil, Purified Water

INFORMATION FOR OWNERS/CAREGIVERS

NDC 10733-173-01

Premier

Topicale GelPatch

Oral Anesthetic Suspension

Benzocaine, 18 %

REF 9007149 Contains: 25 - 0.2gm Packets

Mint

Made in U.S.A.

Manufactured for: Premier® Dental Products Company,

1710 Romano Drive, Plymouth Meeting, PA 19462 U.S.A.

Manufacturer: Medical Products Laboratories, Inc.

9990 Global Road Philadelphia, PA 19115 U.S.A.

0818017 Rev2 MPL 317932

Questions or Comments?

888.670.6100 or 610.239.6000

M-Th: 7:30a.m. - 5:30p.m., F: 7:30a.m. - 4:00p.m. EST

To obtain an SDS, contact Customer Service Department or visit www.premusa.com.

Retain drug facts for future reference.